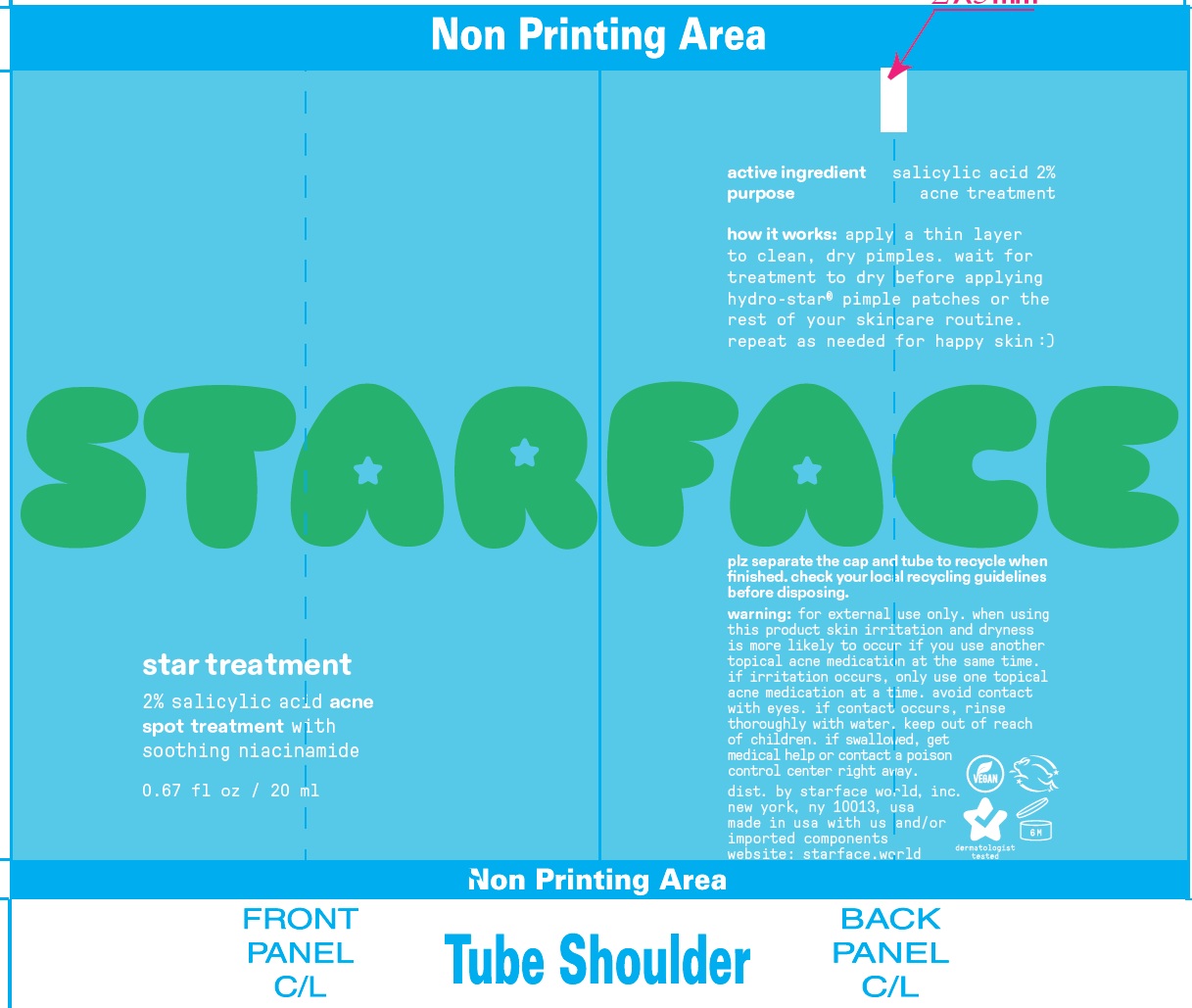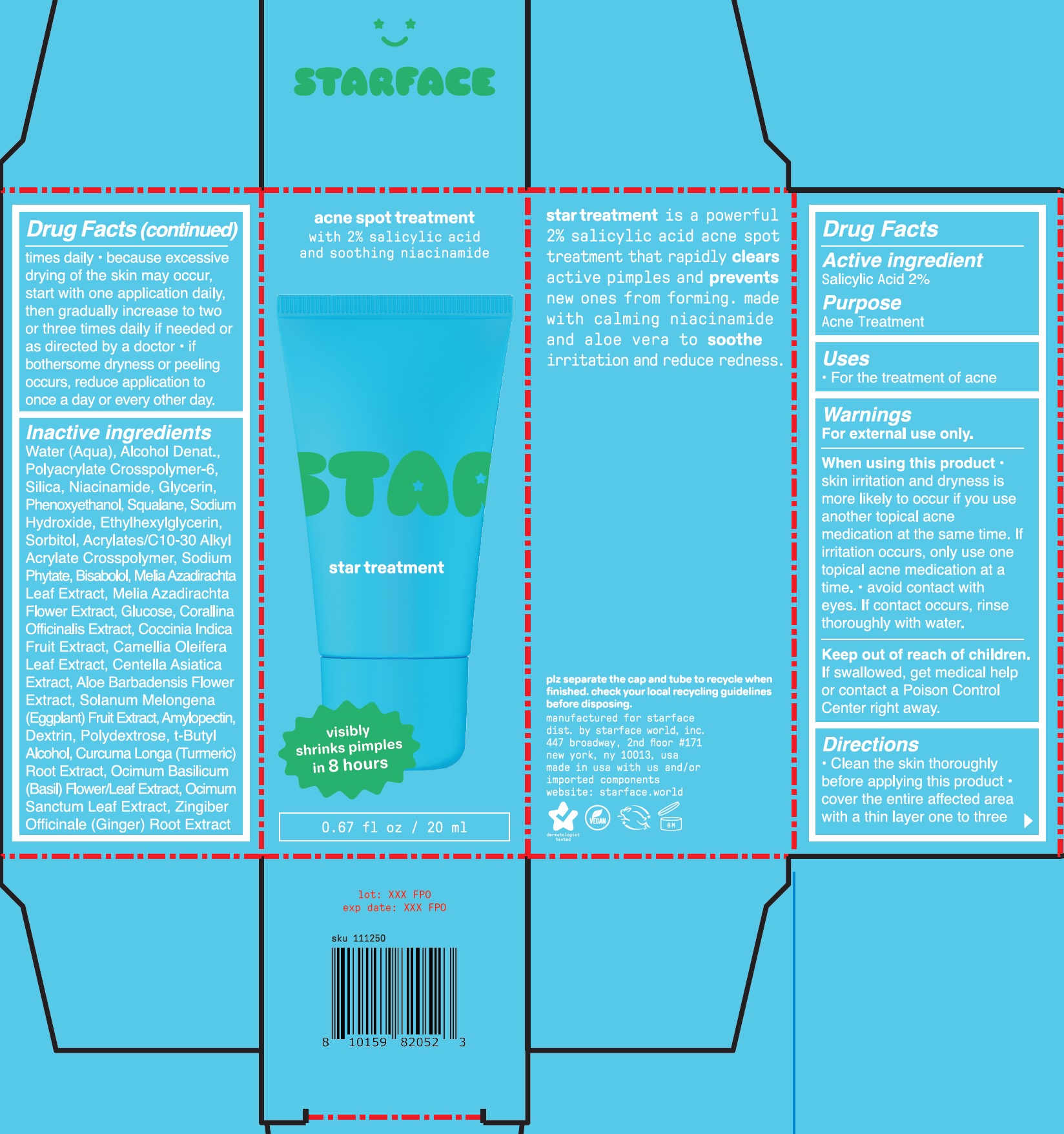 DRUG LABEL: Starface Acne Spot Treatment
NDC: 83171-003 | Form: GEL
Manufacturer: Starface World, Inc.
Category: otc | Type: HUMAN OTC DRUG LABEL
Date: 20251007

ACTIVE INGREDIENTS: SALICYLIC ACID 20 mg/1 mL
INACTIVE INGREDIENTS: DEXTRIN PALMITATE (CORN; 20000 MW); ACRYLATES/C10-30 ALKYL ACRYLATE CROSSPOLYMER (60000 MPA.S); SILICON DIOXIDE; WATER; ALCOHOL; AMMONIUM ACRYLOYLDIMETHYLTAURATE, DIMETHYLACRYLAMIDE, LAURYL METHACRYLATE AND LAURETH-4 METHACRYLATE COPOLYMER, TRIMETHYLOLPROPANE TRIACRYLATE CROSSLINKED (45000 MPA.S); NIACINAMIDE; GLYCERIN; PHENOXYETHANOL; SQUALANE; SODIUM HYDROXIDE; ETHYLHEXYLGLYCERIN; SORBITOL; PHYTATE SODIUM; BISABOLOL; AZADIRACHTA INDICA FLOWER; ANHYDROUS DEXTROSE; CORALLINA OFFICINALIS; COCCINIA GRANDIS FRUIT; CAMELLIA OLEIFERA LEAF; CENTELLA ASIATICA TRITERPENOIDS; ALOE VERA FLOWER; EGGPLANT; POLYDEXTROSE; TERT-BUTYL ALCOHOL; TURMERIC; OCIMUM BASILICUM FLOWERING TOP; HOLY BASIL LEAF; GINGER; AMYLOPECTIN, UNSPECIFIED SOURCE

Starface Acne Spot Treatment

Active ingredient

Salicylic Acid 2%

Purpose

Acne Treatment

Uses

- For the treatment of acne.

Warnings

For external use only.

When using this product

- skin irritattion and dryness is more likely to occur if you use another topical acne medication at the same time. If irritation occurs, only use one topical acne medication at a time.
- avoid contact with eyes. If contact occurs, rinse thoroughly with water.

Keep out of reach of children.

If swallowed, get medical help or contact a Poison Control Center right away.

Directions

- Clean the skin thoroughly before applying this product
- cover the entire affected area with a thin layer one to three times times daily
- because excessive drying of the skin may occur, start with one application daily, then gradually increase to two or three times daily if needed or as directed by a doctor
- if bothersome dryness or peeling occurs, reduce application to once a day or every other day.

Inactive ingredients

Water/Aqua, Alcohol Denat., Polyacrylate Crosspolymer-6, Silica, Niacinamide, Glycerin, Phenoxyethanol, Squalane, Sodium Hydroxide, Ethylhexylglycerin, Sorbitol, Acrylates/C 10-30 Alkyl Acrylate Crosspolymer, Sodium Phytate, Bisabolol, Melia Azadirachta Flower Extract, Glucose, Corallina Officinalis Extract, Coccinia Indica Fruit Extract, Camellia Oleifera Leaf Extract, Centella Asiatica Extract, Aloe Barbadensis Flower Extract, Solanum Melongena (Eggplant) Fruit Extract, Amylopectin, Dextrin, Polydextrose, t-Butyl Alcohol, Curcuma Longa (Turmeric) Root Extract, Ocimum Basilicum (Basil) Flower/Leaf Extract, Ocimum Sanctum Leaf Extract, Zingiber Officinale (Ginger) Root Extract